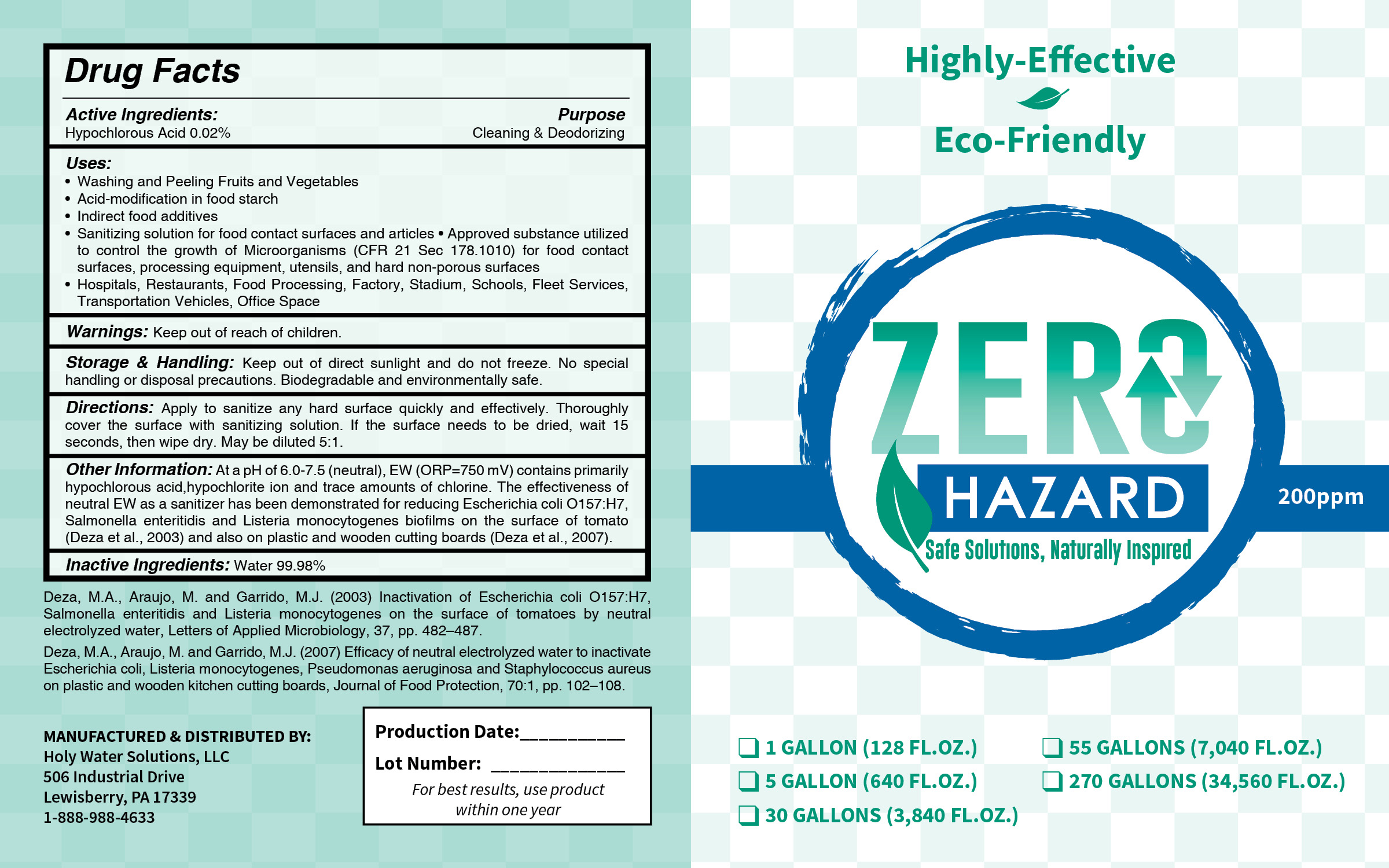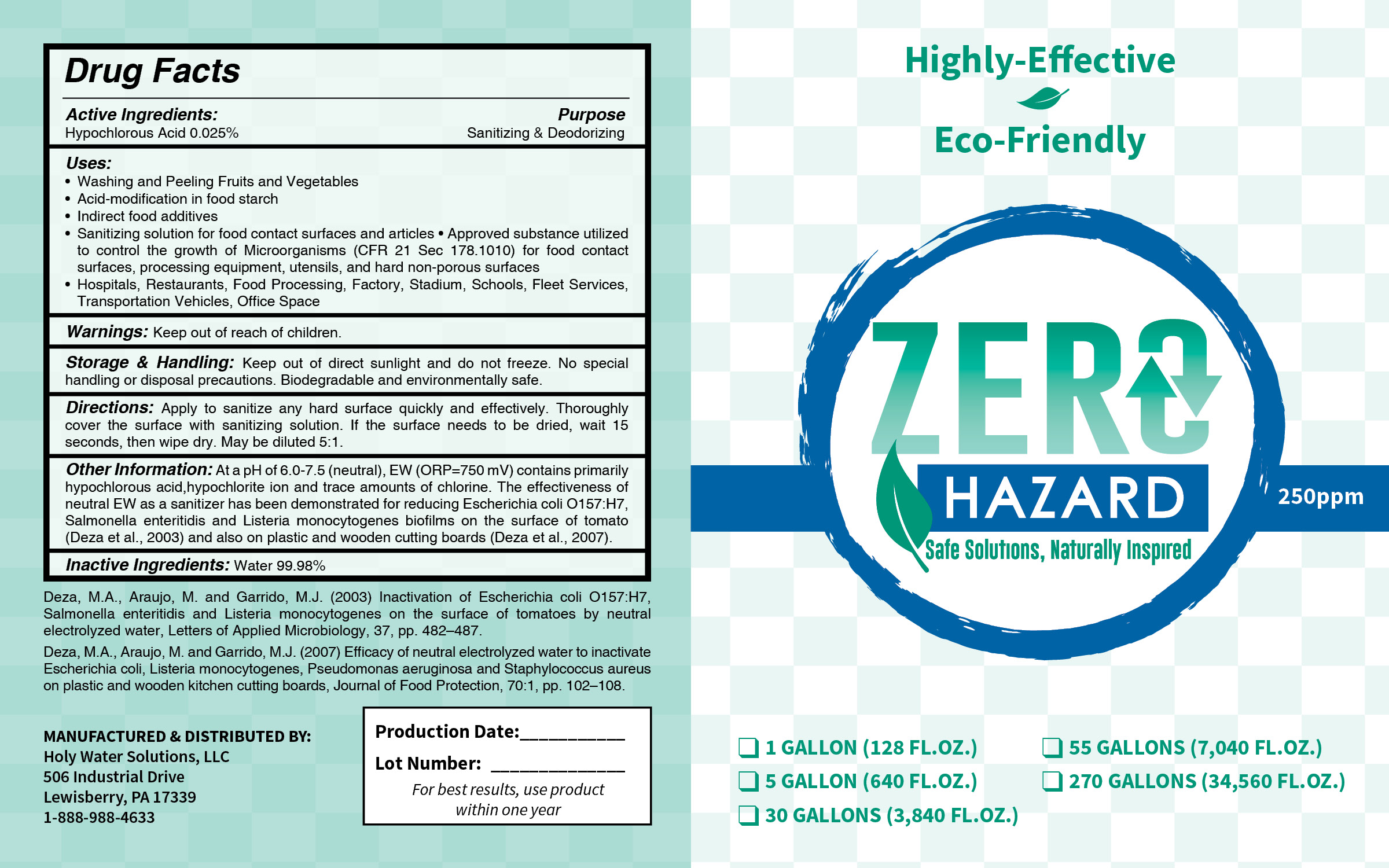 DRUG LABEL: Sanitizer
NDC: 78043-250 | Form: LIQUID
Manufacturer: Holy Water Solutions, LLC
Category: otc | Type: HUMAN OTC DRUG LABEL
Date: 20200526

ACTIVE INGREDIENTS: HYPOCHLOROUS ACID 250 mg/1 L
INACTIVE INGREDIENTS: WATER

Zero Hazard

Directions

Apply to sanitize any hard surface quickly and effectively. Thouroughly cover the surface with sanitizing solution. If the surface needs to be dried, wait 15 seconds, then wipe dry. May be diluted 5:1.

Warnings

Keep out of reach of children

Uses:

- Washing and peeling fruits and vegetables
- Acid-modification in food starch
- Indirect food additives
- Sanitizing solution for food contact surfaces and articles - approved substance utilized to control the growth of Microorganisms (CFR 2 Sec 178.1010) for food contact surfaces, processing equipment, utencils, and hard non-porous surfaces
- Hospitals, restaurants, food processing, factory, stadium, schools, fleet services, transportation vehicles, office space

Storage and Handling

Keep out of direct sunlight and do not freeze. No special handling or disposal precautions. Biodegradable and environmentally safe.

Inactive Ingredients

Water 99.98%

Other Information

At a pH of 6.0-7.5 (neutral), EW (ORP=750mV) contains primarily hypochlorous acid, hypochlorite ion and trace amounts of chlorine. The effectiveness of neutral EW as a sanitizer has been demonstrated for reducing Escherichia coli O157:H7, Salmonella enteritidis and Listeria monocytogenes biofilms on the surface of tomato (Deza et al., 2003) and also on plastic and wooden cutting boards (Deza et al., 2007)

Deza, M.A., Araujo, M. and Garrido, M.J. (2003) Inactivation of Escherichia coli O157:H7, Salmonella enteritidis and Listeria monocytogenes on the surface of tomatoes by neutral electrolyzed water, Letters of Applied Microbiology, 37, pp. 482-487.

Deza, M.A., Araujo, M. and Garrido, M.J. (2007) Efficacy of neutral electrolyzed water to inactivate Escherichia coli, Listeria monocytogenes, Pseudomonas aeruginosa and Staphyloccoccus aureus on plastic and wooden kitchen cutting boards, Journal of Food Protection, 70:1, pp. 102-108

Purpose

Sanitizing & Deodorizing

Active Ingredient

Hypochlourous Acid 0.025%

Warnings

Keep out of reach of children